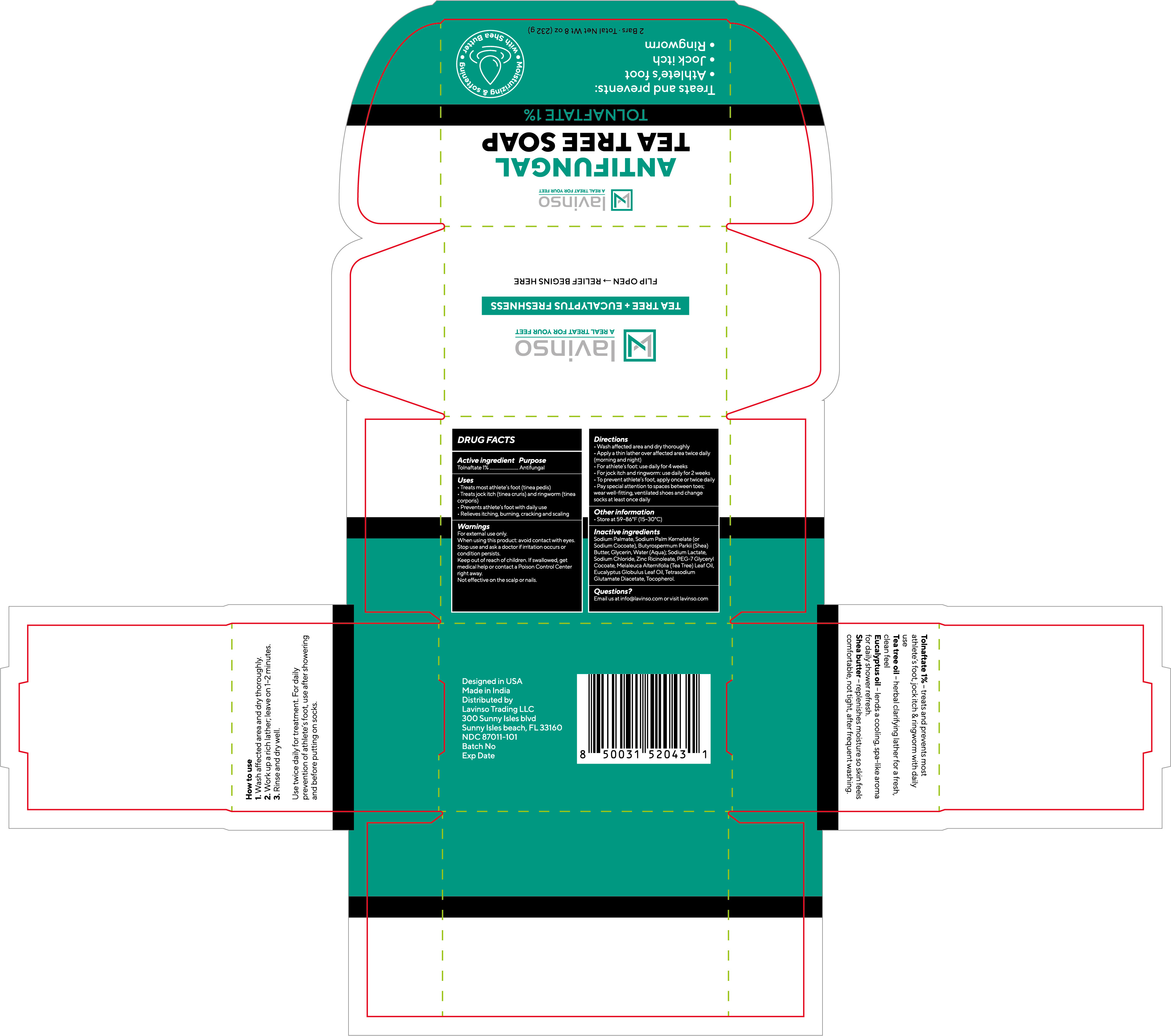 DRUG LABEL: Lavinso Antifungal
NDC: 87011-102 | Form: SOAP
Manufacturer: Lavinso Trading LLC
Category: otc | Type: HUMAN OTC DRUG LABEL
Date: 20251212

ACTIVE INGREDIENTS: TOLNAFTATE 1 g/100 g
INACTIVE INGREDIENTS: ZINC RICINOLEATE; TOCOPHEROL; SODIUM PALMATE; SODIUM PALM KERNELATE; EUCALYPTUS OIL; SODIUM LACTATE; SHEA BUTTER; TEA TREE OIL; GLYCERIN; TETRASODIUM GLUTAMATE DIACETATE; PEG-7 GLYCERYL COCOATE; SODIUM CHLORIDE; WATER

Lavinso Antifungal Tea Trea Soap - Labeling

Active Ingredients

TOLNAFTATE 1%

PURPOSE

Antifungal

Uses

Treats most athlete’s foot (tinea pedis)

Treats jock itch (tinea cruris) and ringworm (tinea corporis)

Prevents athlete’s foot with daily use

Relieves itching, burning, cracking and scaling

Warnings

For external use only

Not effective on the scalp or nails.

How to use

Wash affected area and dry thoroughly.

Work up leather and leave on 1–2 minutes.

Rinse and dry well.

Use twice daily for treatment. For daily prevention of athlete’s foot, use after showering and drying the affected area.

Inactive ingredients

Sodium Palmate, Sodium Palm Kernelate (or Sodium Cocoate), Water, Glycerin, Sodium Lactate, Butylene Glycol, Zinc Ricinoleate, PEG-7 Glyceryl Cocoate, Mica, Titanium Dioxide, Tea Tree Oil, Eucalyptus Globulus Leaf Oil, Tetrasodium Glutamate Diacetate, Tocopherol.

Questions?

Email us at: info@lavinso.com or visit lavinso.com

Directions

Wash affected area and dry thoroughly

Apply a thin layer of the product over affected area twice daily (morning and night)

For athlete's foot and ringworm: use daily for 4 weeks

For jock itch and ringworm: use daily for 2 weeks

To prevent athlete's foot, apply once or twice daily

Pay special attention to spaces between toes

Wear well-fitting, ventilated shoes and change socks at least once daily

Keep out of reach of children. If swallowed, get medical help or contact a Poison Control Center right away.

When using this product: avoid contact with eyes.

Stop use and ask a doctor if: irritation occurs or condition persists.

PACKAGE LABEL

lavinso
A REAL TREAT FOR YOUR FEET

ANTIFUNGAL
TEA TREE SOAP

TOLNAFTATE 1%

Treats and prevents:
• Athlete’s foot
• Jock itch
• Ringworm

Moisturizing & softening
with Shea Butter

2 Bars · Total Net Wt 8 oz (232 g)